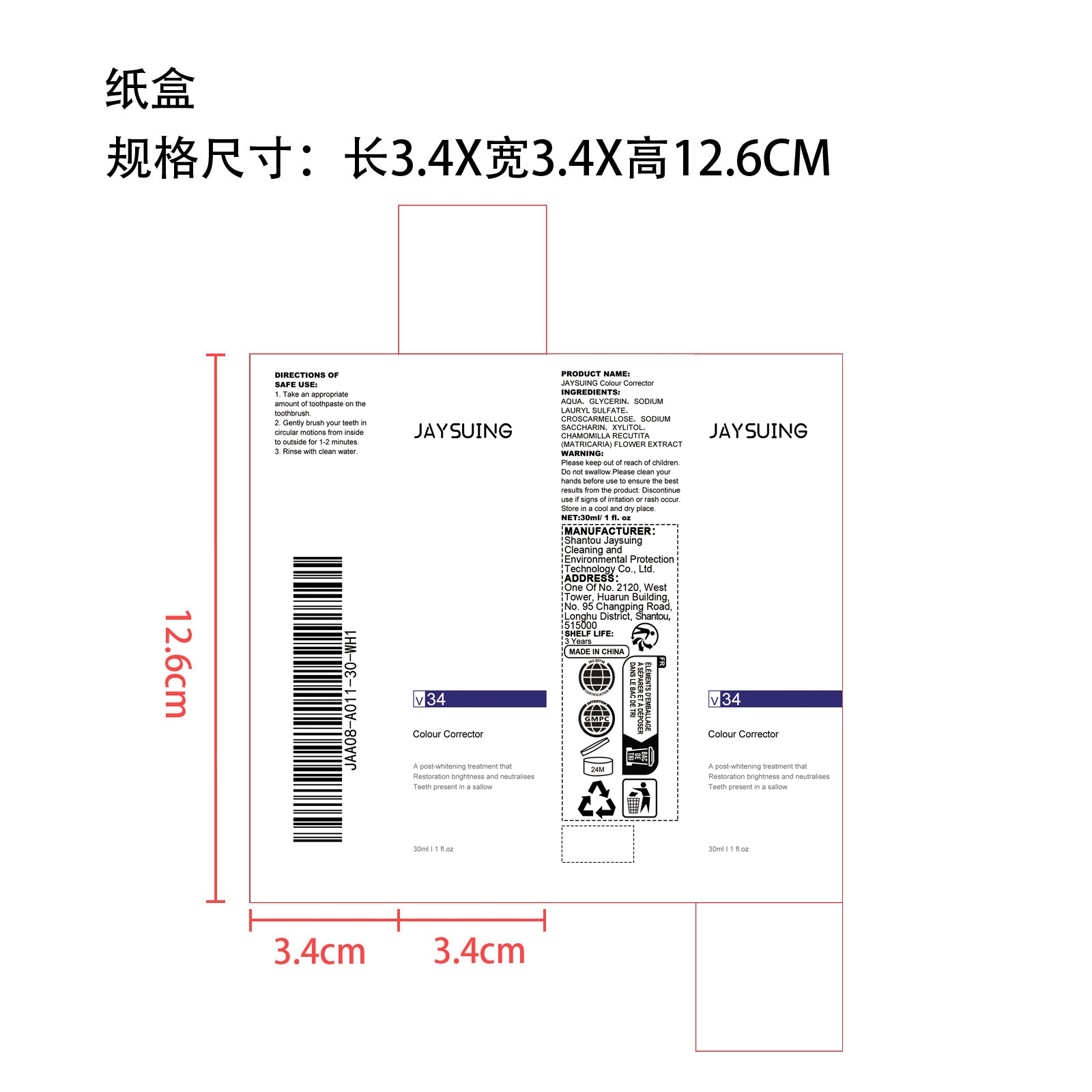 DRUG LABEL: JAYSUING Colour Corrector
NDC: 85060-006 | Form: LIQUID
Manufacturer: Shantou Jaysuing Cleaning and Environmental Protection Technology Co., Ltd.
Category: otc | Type: HUMAN OTC DRUG LABEL
Date: 20251127

ACTIVE INGREDIENTS: CHAMOMILE 0.006 mg/30 mg
INACTIVE INGREDIENTS: AQUA 24.594 mg/30 mg; CROSCARMELLOSE 0.9 mg/30 mg; GLYCERIN 3 mg/30 mg; XYLITOL 0.15 mg/30 mg; SODIUM SACCHARIN 0.15 mg/30 mg; SODIUM LAURYL SULFATE 1.2 mg/30 mg

Active Ingredient(s)

CHAMOMILLA RECUTITA (MATRICARIA) FLOWER EXTRACT

Purpose

Which can effectively clean the mouth, maintain oral hygiene, effectively freshen the breath after use, and keep the mouth moist, fresh and lasting

Use

1.Take an appropriate amount of toothpaste on the toothbrush.

2.Gently brush your teeth in circular motions from inside to outside for 1-2 minutes.

3.Rinse with clean water.

WARNINGS

Please keep out of reach of children. Do not swallow.Please clean your hands before use to ensure the best results from the product. Discontinue use if signs of irritation or rash occur. Store in a cool and dry place.

DO NOT USE

Discontinue use if signs of irritation or rash occur.

STOP USE

Discontinue use if signs of irritation or rash occur.

KEEP OUT OF REACH OF CHILDREN

Please keep out of reach of children. Do not swallow.

STORAGE AND HANDLING

Please keep out of reach of children. Do not swallow.

INACTIVE INGREDIENT

AQUA、GLYCERIN、SODIUM LAURYL SULFATE、CROSCARMELLOSE、SODIUM SACCHARIN、XYLITOL

INDICATIONS AND USAGE

1.Take an appropriate amount of toothpaste on the toothbrush.

2.Gently brush your teeth in circular motions from inside to outside for 1-2 minutes.

3.Rinse with clean water.

DOSAGE AND ADMINISTRATION

1.Take an appropriate amount of toothpaste on the toothbrush.

2.Gently brush your teeth in circular motions from inside to outside for 1-2 minutes.

3.Rinse with clean water.